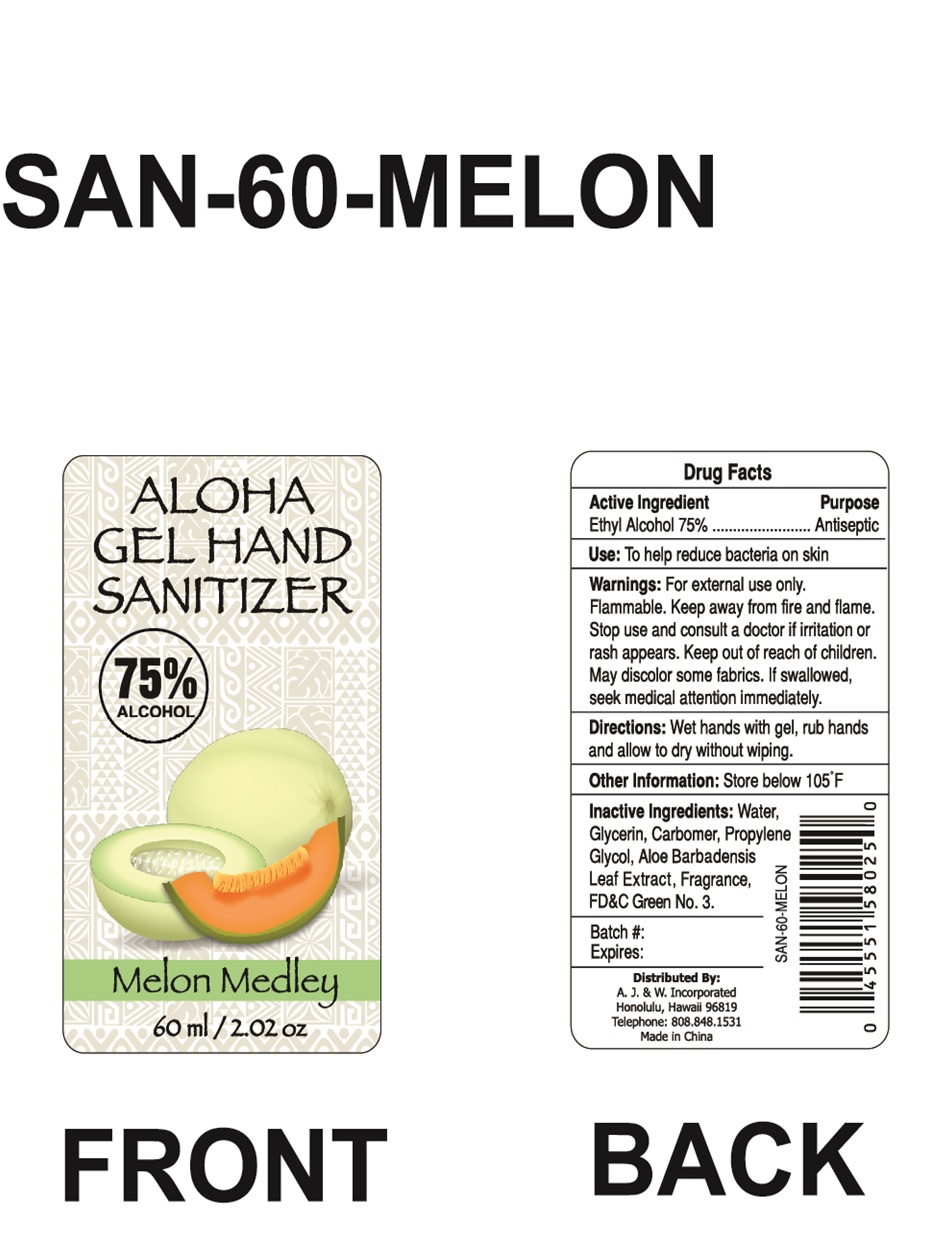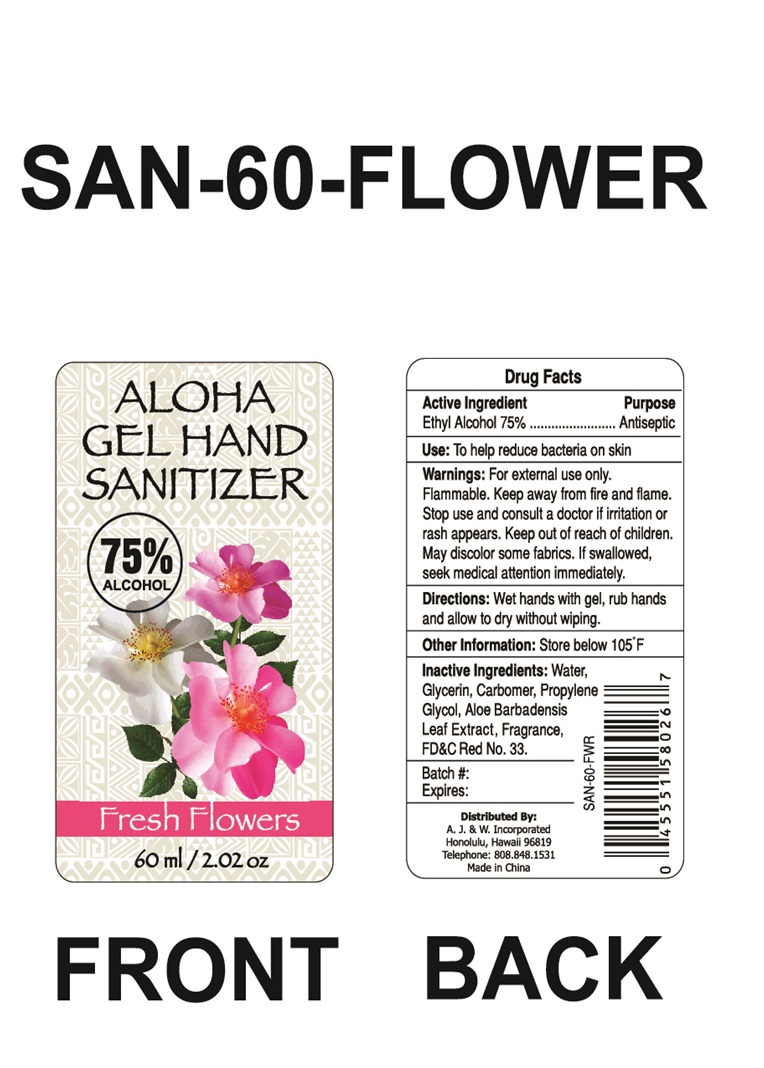 DRUG LABEL: Gel Hand sanitizer
NDC: 75742-016 | Form: GEL
Manufacturer: Zhejiang Guoyao Jingyue Aerosol Co., Ltd.
Category: otc | Type: HUMAN OTC DRUG LABEL
Date: 20200915

ACTIVE INGREDIENTS: ALCOHOL 75 mL/100 mL
INACTIVE INGREDIENTS: CARBOMER HOMOPOLYMER, UNSPECIFIED TYPE; PROPYLENE GLYCOL; ALOE VERA LEAF; FD&C GREEN NO. 3; GLYCERIN; WATER; D&C RED NO. 33

ALOHA GEL HAND SANITIZER

Active Ingredient

Ethyl Alcohol 75% v/v

Purpose

Antiseptic

Uses

To help reduce bacteria on the skin.

Warnings

For external use only. Flammable, keep away from fire and flame. May discolor certain fabrics

Warnings

Stop use and consult a doctor if irritation or rash appears

Warnings

Keep out of reach of children.

Warnings

If swallowed, seek medical attention immediately.

Directions

Wet hands thoroughly with gel, rub vigorously and allow to dry without wiping.

Other information

Store below 105°F.

Inactive Ingredients:

(SAN-60-MELON, NDC CODE: 75742-016-01)

Water, Glycerin, Carbomer, Propylene Glycol, Aloe Barbadensis Leaf Extract, Fragrance, FD&C Green No. 3

(SAN-60-FLOWER, NDC CODE: 75742-016-02)

Water, Glycerin, Carbomer, Propylene Glycol, Aloe Barbadensis Leaf Extract, Fragrance, D&C Green No. 33